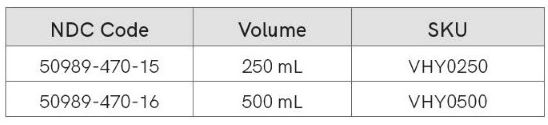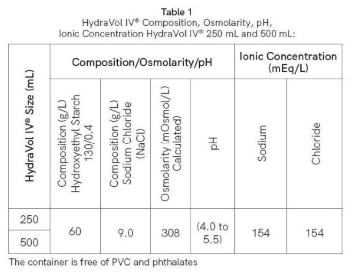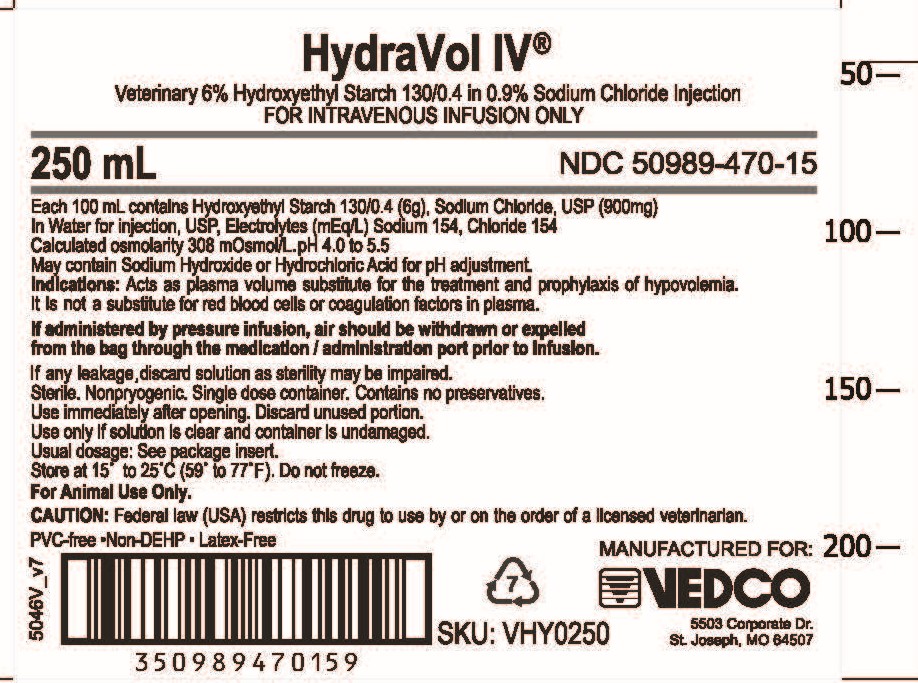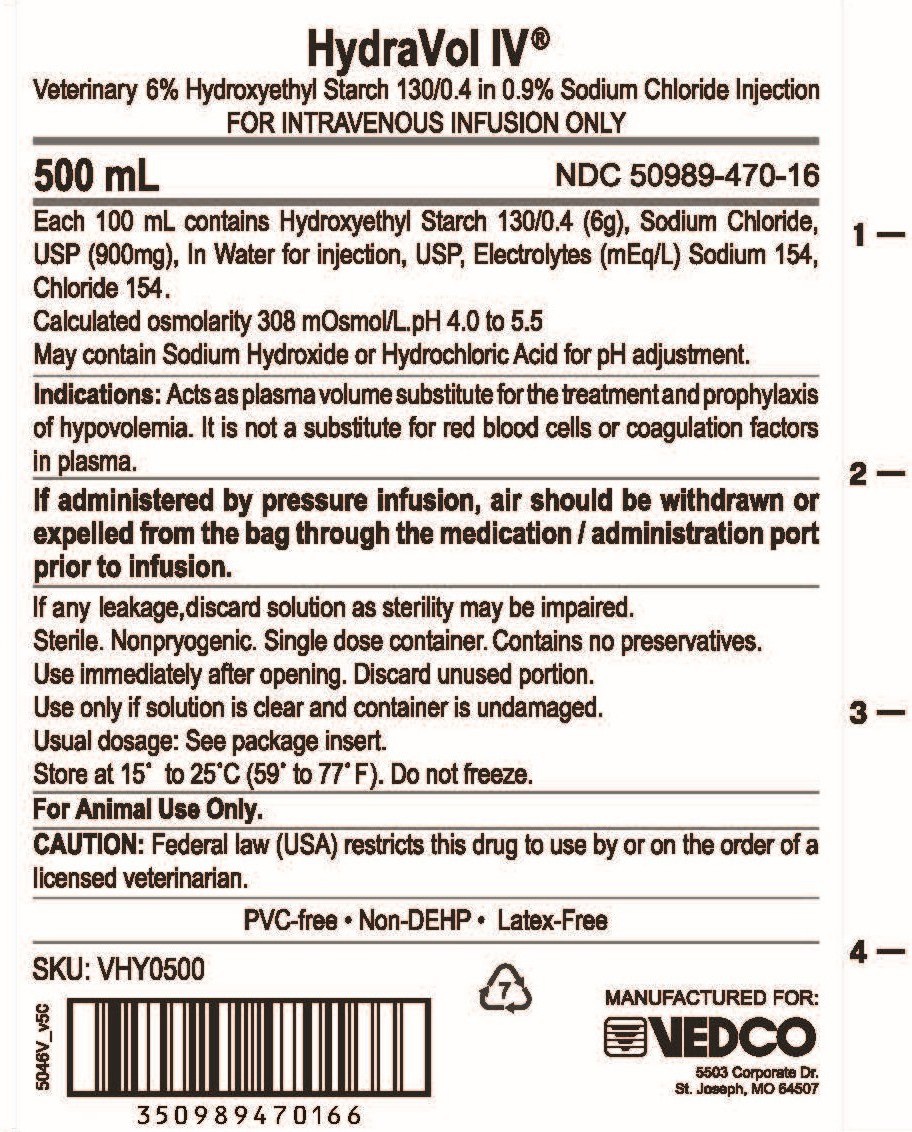 DRUG LABEL: HydraVol IV
NDC: 50989-470 | Form: INJECTION
Manufacturer: VEDCO INC
Category: animal | Type: PRESCRIPTION ANIMAL DRUG LABEL
Date: 20260223

ACTIVE INGREDIENTS: HYDROXYETHYL STARCH 130/0.4 6 g/100 mL

HydraVol IV®

Caution: Federal Law restricts this drug to use by or on the order of a licensed veterinarian

Sterile Nonpyrogenic Solution

For Animal Use only

Description:

HydraVol IV® (6% hydroxyethyl starch 130/0.4 in 0.9% sodium chloride injection) is a sterile, non-pyrogenic solution indicated for the treatment and prophylaxis of hypovolemia. It is not a substitute for red blood cells or coagulation factors in plasma. May be administered via intravenous infusion using aseptic technique. It contains no antimicrobial agents.

Clinical Pharmacology:

HydraVol IV® acts as a plasma volume substitute for the treatment and prophylaxis of hypovolemia. It is not a substitute for red blood cells or coagulation factors in plasma.

Contraindications:

The use of HydraVol IV® is contraindicatedin the following conditions:

- Known hypersensitivity to hydroxyethyl starch.
- Fluid overload (hyperhydration) and especially in cases of pulmonary edema and congestive heart failure.
- Renal failure with oliguria or anuria not related to hypovolemia.
- Patients receiving dialysis treatment.
- Sever hypernatremia or severe hyperchloremia.
- Intracranial bleeding.

Warnings:

Anaphylactoid reactions (bradycardia, tachycardia, bronchospasm, non-cardiac pulmonary edema) have been reported with solutions containing hydroxyethyl starch. If a hypersensitivity reaction occurs, administration of the drug should be discontinued immediately, and the appropriate treatment and supportive measures should be undertaken until symptoms have resolved.

Fluid status and rate of infusion should be assessed regularly during treatment, especially in patients with cardiac insufficiency or severe kidney dysfunction.

In cases of severe dehydration, a crystalloid solution should be given first. Generally, sufficient fluid should be administered in order to avoid dehydration.

Caution should be observed before administering HydraVol IV® to patients with severe liver disease or severe bleeding disorders. With the administration of certain hydroxyethyl starch solutions, disturbances of blood coagulation can occur depending on the dosage.

If administered by pressure infusion, air should be withdrawn or expelled from the bag through the administration port prior to infusion.

Do not introduce additives into this container.

Adverse Reactions:

- Products containing hydroxyethyl starch may lead to anaphylactoid/hypersensitivity reactions.
- Prolonged administrations of high doses of Hydroxyethyl starch may cause pruritis (itching), hemodilution (resulting in dilution of blood components, e.g., coagulation factors and other plasma proteins, and in a decrease in hematocrit).
- If an adverse reaction does occur, discontinue the infusion and evaluate the patient, institute appropriate therapeutic countermeasures and save the remainder of the fluid for examination, if deemed necessary.

Precautions:

- Do not administer unless solution is clear and seal is intact.
- This is a single dose unit. It contains no preservatives.
- Use entire contents when first opened.
- Clinical evaluation and periodic laboratory determinations are necessary to monitor changes in fluid balance, electrolyte concentrations, and acid base balance during prolonged parenteral therapy, or whenever the patient's condition warrants such evaluation.

Drug Interactions:

No interactions with other drugs or nutritional products are known. The safety and compatibility of additives have not been established.

Dosage and Administration:

- To be used as directed by a licensed veterinarian. HydraVol IV® is administered by intravenous infusion only. The daily dose and rate of infusion depend on the patient's blood loss, on the maintenance or restoration of hemodynamics and on the hemodilution (dilution effect).
- For use in one patient on one occasion only. Discard any unused portion. Care should be taken with administration technique to avoid administration site reactions and infection.
- HydraVol IV® can be administered repetitively over several days. The initial 10-20 mL should be infused slowly, keeping the patient under close observation due to possible anaphylactoid reactions. See Warnings and Precautions.

ADULT DOSE

- As a general recommendation, the class of synthetic colloids are prescribed at doses up to 20 mL per kg of body weight per day in small animal patients.^1 In a 30 kg patient, this is a dose of 600 mL of HydraVol IV® (equivalent to 1.2 g hydroxyethyl starch and 3.1 mEq sodium per kg of body weight).

Overdosage:

As with all plasma volume substitutes, overdosage can lead to overloading of the circulatory system (e.g., pulmonary edema). In this case, the infusion should be stopped immediately and, if necessary, a diuretic should be administered. See Warnings and Precautions.

Directions for Use of Plastic Container:

To open

Tear the overwrp and remove the solution container. Some opacity of the plastic due to moisture absorption during the sterilization process may be observed. This is normal and does not affect the solution quality or safety. The opacity will diminish gradually. Check for minute leaks by squeezing inner bag firmly. If leaks are found, discard solution as sterility may be impaired.

Preparation for administration

1. Suspend container from eyelet support.
2. Remove foil seal from inlet port to inject and remove twist off tab from the outlet port to administer the solution located at the bottom of this container.
3. Attach administration set.

Warning: Do not introduce additives into this container.

Sorage:

Store at 15°C to 25°C (59°F to 77°F). Do not freeze.

How Supplied:

HydraVol IV® (6% hydroxyethyl starch 130/0.4 in 0.9% sodium chloride injection) for intravenous infusion is supplied in the following primary container: Polyolefin bag with overwrap: 250 mL and 500 mL.

Manufactured For:

Vedco, Inc.

5503 Corporate Dr.

St. Joseph, MO 64507 USA

For a copy of the Safety Data Sheet (SDS) or to report adverse reactions call Vedco, Inc. customer service (888) 708-3326.

References

1. Silverstein D, Hopper K. Small Animal Critical Care Medicine. (2009)

PACKAGE LABEL

HydraVol IV®

Veterinary 6% Hydroxyethyl Starch 130/0.4 in 0.9% Sodium Chloride Injection

FOR INTRAVENOUS INFUSION ONLY